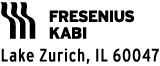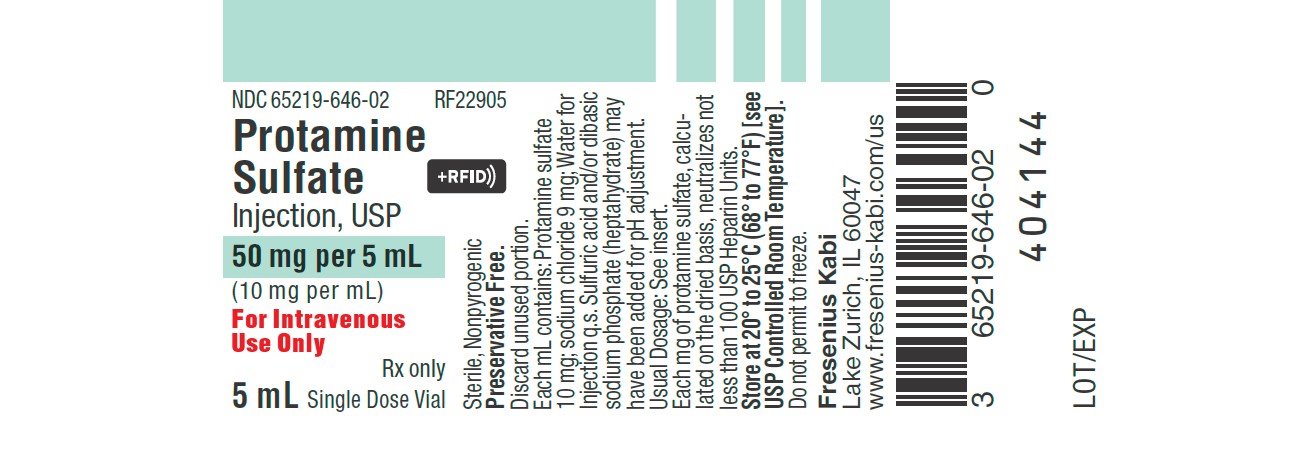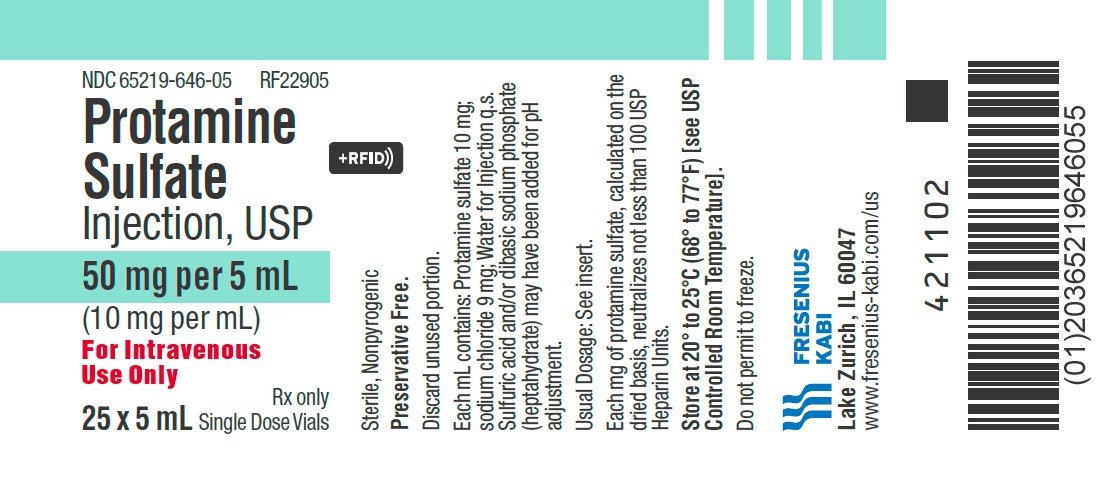 DRUG LABEL: Protamine Sulfate
NDC: 65219-646 | Form: INJECTION, SOLUTION
Manufacturer: Fresenius Kabi USA, LLC
Category: prescription | Type: HUMAN PRESCRIPTION DRUG LABEL
Date: 20250429

ACTIVE INGREDIENTS: PROTAMINE SULFATE 10 mg/1 mL
INACTIVE INGREDIENTS: SODIUM CHLORIDE 9 mg/1 mL; SULFURIC ACID; SODIUM PHOSPHATE, DIBASIC, UNSPECIFIED FORM; WATER

Protamine Sulfate Injection, USP

For Intravenous Use

Rx only

WARNING

Protamine sulfate can cause severe hypotension, cardiovascular collapse, noncardiogenic pulmonary edema, catastrophic pulmonary vasoconstriction, and pulmonary hypertension. Risk factors include high dose or overdose, rapid administration (see WARNINGS and DOSAGE AND ADMINISTRATION), repeated doses, previous administration of protamine, and current or previous use of protamine-containing drugs (NPH insulin, protamine zinc insulin, and certain beta-blockers). Allergy to fish, previous vasectomy, and severe left ventricular dysfunction and abnormal preoperative pulmonary hemodynamics also may be risk factors. In patients with any of these risk factors, the risk to benefit of administration of protamine sulfate should be carefully considered. Vasopressors and resuscitation equipment should be immediately available in case of a severe reaction to protamine. Protamine sulfate should not be given when bleeding occurs without prior heparin use.

DESCRIPTION:

Protamines are simple proteins of low molecular weight that are rich in arginine and strongly basic. They occur in the sperm of salmon and certain other species of fish.

Protamine sulfate occurs as fine white or off-white amorphous or crystalline powder. It is sparingly soluble in water. The pH is between 6.0 and 7.0. The cationic hydrogenated protamine at a pH of 6.8 to 7.1 reacts with anionic heparin at a pH of 5.0 to 7.5 to form an inactive complex.

Protamine Sulfate Injection, USP is a sterile, isotonic solution of protamine sulfate. It acts as a heparin antagonist. It is also a weak anticoagulant.

Each mL contains: Protamine sulfate 10 mg; sodium chloride 9 mg; Water for Injection q.s. Sulfuric acid and/or dibasic sodium phosphate (heptahydrate) may have been added for pH adjustment.

The preparation is preservative free.

Protamine sulfate is administered intravenously.

CLINICAL PHARMACOLOGY:

When administered alone, protamine has an anticoagulant effect. However, when it is given in the presence of heparin (which is strongly acidic), a stable salt is formed and the anticoagulant activity of both drugs is lost.

Protamine sulfate has a rapid onset of action. Neutralization of heparin occurs within five minutes after intravenous administration of an appropriate dose of protamine sulfate. Although the metabolic fate of the heparin-protamine complex has not been elucidated, it has been postulated that protamine sulfate in the heparin-protamine complex may be partially metabolized or may be attacked by fibrinolysin, thus freeing heparin.

INDICATIONS AND USAGE:

Protamine Sulfate Injection, USP is indicated in the treatment of heparin overdosage.

CONTRAINDICATIONS:

Protamine sulfate is contraindicated in patients who have shown previous intolerance to the drug.

WARNINGS:

Hyperheparinemia or bleeding has been reported in experimental animals and in some patients 30 minutes to 18 hours after cardiac surgery (under cardiopulmonary bypass) in spite of complete neutralization of heparin by adequate doses of protamine sulfate at the end of the operation. It is important to keep the patient under close observation after cardiac surgery. Additional doses of protamine sulfate should be administered if indicated by coagulation studies, such as the heparin titration test with protamine and the determination of plasma thrombin time.

Too-rapid administration of protamine sulfate can cause severe hypotensive and anaphylactoid reactions (see DOSAGE AND ADMINISTRATION and WARNINGS). Facilities to treat shock should be available.

PRECAUTIONS:

General

Because of the anticoagulant effect of protamine, it is unwise to give more than 50 mg over a short period unless a larger dose is clearly needed.

Patients with a history of allergy to fish may develop hypersensitivity reactions to protamine, although to date no relationship has been established between allergic reactions to protamine and fish allergy.

Previous exposure to protamine can induce a humoral immune response and predispose susceptible individuals to the development of untoward reactions from the subsequent use of this drug. Patients exposed to protamine through the use of protamine-containing insulin or during heparin neutralization may experience life-threatening reactions and fatal anaphylaxis upon receiving large doses of protamine intravenously. Severe reactions to intravenous protamine can occur in the absence of local or systemic allergic reactions to subcutaneous injection of protamine-containing insulin. Reports of the presence of antiprotamine antibodies in the sera of infertile or vasectomized men suggest that some of these individuals may react to the use of protamine sulfate.

Fatal anaphylaxis has been reported in one patient with no prior history of allergies.

Drug Interactions

Protamine sulfate has been shown to be incompatible with certain antibiotics, including several of the cephalosporins and penicillins (see DOSAGE AND ADMINISTRATION).

Carcinogenesis, Mutagenesis, Impairment of Fertility

Studies have not been performed to determine potential for carcinogenicity, mutagenicity or impairment of fertility.

Pregnancy

Pregnancy Category C
Animal reproduction studies have not been conducted with protamine sulfate. It is also not known whether protamine sulfate can cause fetal harm when administered to a pregnant woman or can affect reproduction capacity. Protamine sulfate should be given to a pregnant woman only if clearly needed.

Nursing Mothers

It is not known whether this drug is excreted in human milk. Because many drugs are excreted in human milk, caution should be exercised when protamine sulfate is administered to a nursing woman.

Pediatric Use

Safety and effectiveness in children have not been established.

ADVERSE REACTIONS:

To report SUSPECTED ADVERSE REACTIONS, contact Fresenius Kabi USA, LLC at 1-800-551-7176 or FDA at 1-800-FDA-1088 or www.fda.gov/medwatch.

The intravenous administration of protamine sulfate may cause a sudden fall in blood pressure and bradycardia. Other reactions include transitory flushing and feeling of warmth, dyspnea, nausea, vomiting and lassitude. Back pain has been reported in conscious patients undergoing such procedures as cardiac catheterization.

Severe adverse reactions have been reported including: (1) Anaphylaxis that resulted in severe respiratory distress, circulation collapse and capillary leak (see PRECAUTIONS). Fatal anaphylaxis has been reported in one patient with no prior history of allergies; (2) Anaphylactoid reactions with circulatory collapse, capillary leak, and noncardiogenic pulmonary edema; acute pulmonary hypertension.

Complement activation by the heparin-protamine complexes, release of lysosomal enzymes from neutrophils, and prostaglandin and thomboxane generation have been associated with the development of anaphylactoid reactions.

Severe and potentially irreversible circulatory collapse associated with myocardial failure and reduced cardiac output can also occur. The mechanism(s) of this reaction and the role played by concurrent factors are unclear.

High-protein, noncardiogenic pulmonary edema associated with the use of protamine has been reported in patients on cardiopulmonary bypass who are undergoing cardiovascular surgery. The etiologic role of protamine in the pathogenesis of this condition is uncertain, and multiple factors have been present in most cases. The condition has been reported in association with administration of certain blood products, other drugs, cardiopulmonary bypass alone, and other etiologic factors. It is difficult to treat, and it can be life-threatening. Because fatal anaphylactic and anaphylactoid reactions have been reported after the administration of protamine sulfate, the drug should be given only when resuscitation techniques and treatment of anaphylactic and anaphylactoid shock are readily available.

OVERDOSAGE:

Signs and Symptoms

Overdose of protamine sulfate may cause bleeding. Protamine has a weak anticoagulant effect due to an interaction with platelets and with many proteins including fibrinogen. This effect should be distinguished from the rebound anticoagulation that may occur 30 minutes to 18 hours following the reversal of heparin with protamine.

Rapid administration of protamine is more likely to result in bradycardia, dyspnea, a sensation of warmth, flushing, and severe hypotension. Hypertension has also occurred.

The median lethal dose of protamine sulfate is 50 mg/kg in mice. Serum concentrations of protamine sulfate are not clinically useful. Information is not available on the amount of drug in a single dose that is associated with overdosage or is likely to be life-threatening.

Treatment

To obtain up-to-date information about the treatment of overdose, a good resource is your certified Regional Poison Control Center. Telephone numbers of certified poison control centers are listed in the Physicians' Desk Reference (PDR). In managing overdosage, consider the possibility of multiple drug overdoses, interaction among drugs and unusual drug kinetics in your patient.

Replace blood loss with blood transfusions or fresh frozen plasma.

If the patient is hypotensive, consider fluids, epinephrine, dobutamine or dopamine.

DOSAGE AND ADMINISTRATION:

Each mg of protamine sulfate, calculated on the dried basis, neutralizes not less than 100 USP Heparin Units.

Protamine sulfate injection should be given by very slow intravenous injection over a 10-minute period in doses not to exceed 50 mg (see WARNINGS).

Protamine sulfate is intended for injection without further dilution; however, if further dilution is desired, D5-W or normal saline may be used. Diluted solutions should not be stored since they contain no preservative.

Protamine sulfate should not be mixed with other drugs without knowledge of their compatibility, because protamine sulfate has been shown to be incompatible with certain antibiotics, including several of the cephalosporins and penicillins.

Because heparin disappears rapidly from the circulation, the dose of protamine sulfate required also decreases rapidly with the time elapsed following intravenous injection of heparin. For example, if the protamine sulfate is administered 30 minutes after the heparin, one-half the usual dose may be sufficient.

The dosage of protamine sulfate should be guided by blood coagulation studies (see WARNINGS).

Parenteral drug products should be visually inspected for particulate matter and discoloration prior to administration, whenever solution and container permit.

HOW SUPPLIED:

Product Code | Unit of Sale | Strength | Each
22905 | NDC 63323-229-05 Unit of 25 | 50 mg per 5 mL (10 mg per mL) | NDC 63323-229-01 5 mL Single Dose Flip-top Vial
RF22905 | NDC 65219-646-05 Unit of 25 | 50 mg per 5 mL (10 mg per mL) | NDC 65219-646-02 5 mL Single Dose Flip-top Vial This product contains an RFID.
22930 | NDC 63323-229-30 Individually Packaged | 250 mg per 25 mL (10 mg per mL) | NDC 63323-229-30 25 mL Single Dose Flip-top Vial

Store at 20° to 25°C (68° to 77°F) [see USP Controlled Room Temperature]. Do not permit to freeze.

CAUTION: The total dose of protamine sulfate contained in product No. 22925 and 22930 (250 mg in 25 mL) is 5 times greater than in product No. 22905 and product No. RF22905 (50 mg in 5 mL).

The large size 25 mL vials are designed for antiheparin treatment only when large doses of heparin have been given during surgery and are to be neutralized by large doses of protamine sulfate after surgical procedures.

www.fresenius-kabi.com/us
45848J

November 2024

PACKAGE LABEL - PRINCIPAL DISPLAY - Protamine 5 mL Single Dose Vial Label

NDC 65219-646-02 RF22905

Protamine

Sulfate

Injection, USP

50 mg per 5 mL

(10 mg per mL)

For Intravenous

Use Only

Rx only

5 mL Single Dose Vial

PACKAGE LABEL - PRINCIPAL DISPLAY - Protamine 5 mL Single Dose Vial Tray Label

NDC 65219-646-05 RF22905

Protamine

Sulfate

Injection, USP

50 mg per 5 mL

(10 mg per mL)

For Intravenous

Use Only

Rx only

25 x 5 mL Single Dose Vials